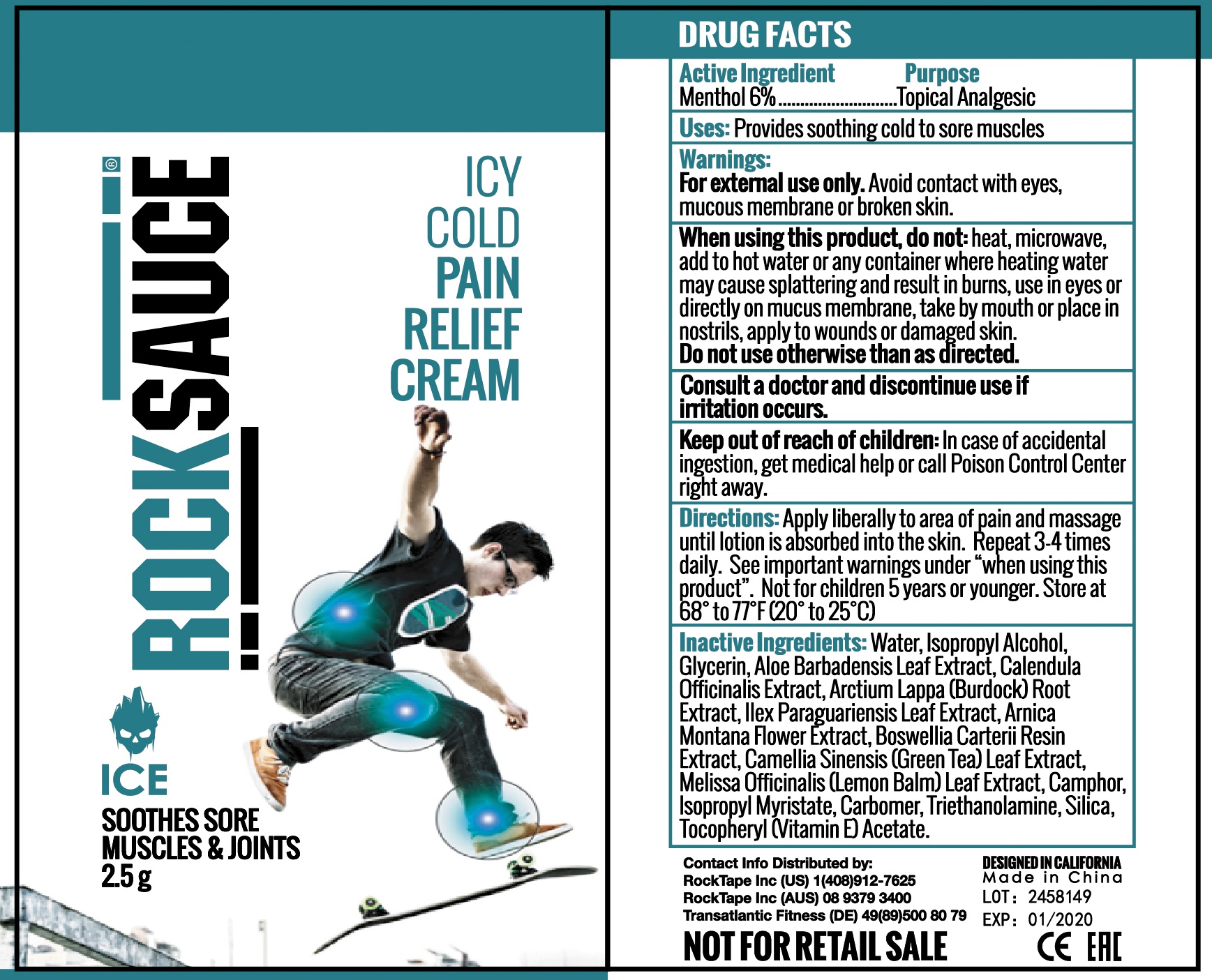 DRUG LABEL: RockSauce ICE
NDC: 73344-101 | Form: GEL
Manufacturer: NINGBO SANTE YING MEDICALAND HEALTHDEVELOPMENT CO.,LTD
Category: otc | Type: HUMAN OTC DRUG LABEL
Date: 20190929

ACTIVE INGREDIENTS: MENTHOL 6.0 g/100 g
INACTIVE INGREDIENTS: WATER; ISOPROPYL ALCOHOL; GLYCERIN; ARCTIUM LAPPA ROOT OIL; ARNICA MONTANA FLOWER; MELISSA OFFICINALIS LEAF OIL; ISOPROPYL MYRISTATE

rocksauce ICE

Active Ingredient

Menthol 6.0%

Purpose

Topical Analgesic

Uses

Provides soothing cold to sore muscles

Warnings

For external use only.

Avoid contact with eyes, mucous membrane or broken skin.

When using this product:

do not: heat, microwave, add to hot water or any container where heating water may cause splattering and result in burns, use in eyes or directly on mucus membane, take by mouth or place in nostrils, apply to wounds or damaged skin.

Do not use otherwise than as directed.

Consult a doctor and discontinue use

if irritation occurs.

Keep out of reach of children.

In case of accidental ingestion, get medical help or call a Poison Control Center right away.

Directions

Apply liberally to area of pain and massage until lotion is absorbed into the skin. Repeat 3-4 times daily. See important warnings under "When using this product". Not for childern 5 years or younger. Store at 68° to 77°F (20° to 25°C).

Inactive Ingredients

Water, Isopropyl Alcohol, Glycerin, Aloe Barbadensis Leaf Extract, Calendula Officinalis Extract, Arctium Lappa (Burdock) Root Extract, Ilex Paraguariensis Leaf Extract, Arnica MOntana Flower Extract, Boswellia Carterii Resin Extract, Camellia Sinensis (Green Tea) Leaf Extract, Melissa Officinalis (Lemon Balm) Leaf Extract, Camphor, Isopropyl Myristate, Carbomer, Triethanolamine, Silica, Tocopheryl (Vitamin E) Acetate

PACKAGE LABEL

RockSauce ICE

Net wt 2.5g

Icy cold pain relief cream

Soothies sore muscles and joints

DISTRIBUTED BY:

Rocktape, Inc

questions: please contact 408-912-7625

made in china